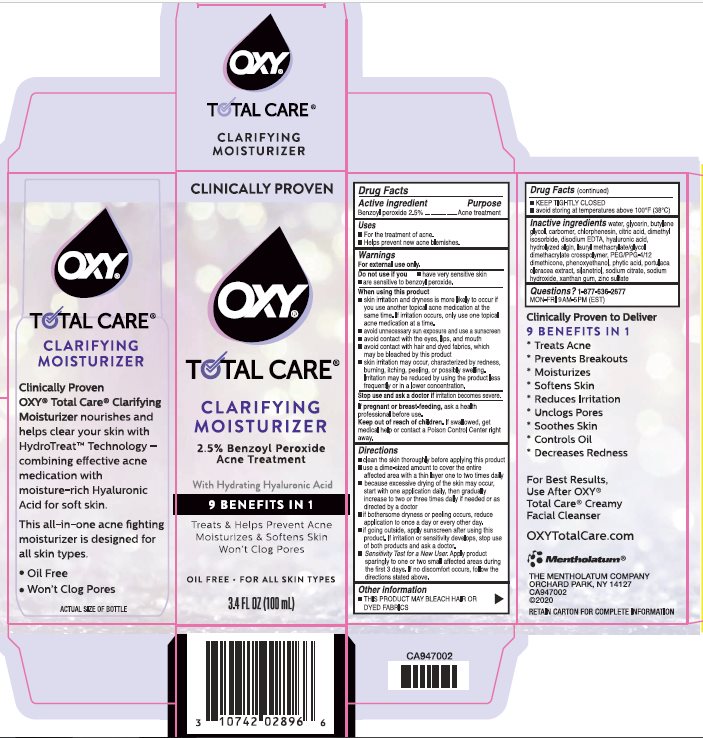 DRUG LABEL: Oxy
NDC: 10742-1314 | Form: LOTION
Manufacturer: The Mentholatum Company
Category: otc | Type: HUMAN OTC DRUG LABEL
Date: 20241213

ACTIVE INGREDIENTS: BENZOYL PEROXIDE 25 mg/1 mL
INACTIVE INGREDIENTS: EDETATE DISODIUM; HYALURONIC ACID; ALGINIC ACID; LAURYL METHACRYLATE/GLYCOL DIMETHACRYLATE CROSSPOLYMER; PEG/PPG-4/12 DIMETHICONE; PHENOXYETHANOL; FYTIC ACID; PURSLANE; SILANETRIOL; TRISODIUM CITRATE DIHYDRATE; SODIUM HYDROXIDE; XANTHAN GUM; ZINC SULFATE HEPTAHYDRATE; WATER; GLYCERIN; BUTYLENE GLYCOL; CARBOXYPOLYMETHYLENE; CHLORPHENESIN; ANHYDROUS CITRIC ACID; DIMETHYL ISOSORBIDE

Drug Facts - OXY Total Care Clarifying Moisturizer

Active ingredient

Benzoyl peroxide 2.5%

Purpose

Benzoyl peroxide – Acne treatment

Keep Out of Reach of Children

If swallowed, get medical help or contact a Poison Control Center right away.

Uses

- For the treatment of acne.
- Helps prevent new acne blemishes.

Warnings

For external use only.

Do not use if you

- have very sensitive skin
- are sensitive to benzoyl peroxide.

When using this product

- skin irritation and dryness is more likely to occur if you use another topical acne medication at the same time. If irritation occurs, use only one topical acne medication at a time.
- avoid unnecessary sun exposure and use a sunscreen
- avoid contact with the eyes, lips, and mouth
- avoid contact with hair and dyed fabrics, which may be bleached by this product
- skin irritation may occur, characterized by redness, burning, itching, peeling, or possibly swelling. Irritation may be reduced by using the product less frequently or in a lower concentration.

Stop use and ask a doctor if irritation becomes severe.

If pregnant or breast-feeding, ask a health professional before use.

Directions

- clean the skin thoroughly before applying this product
- use a dime-sized amount to cover the entire affected area with a thin layer one to two times daily
- because excessive drying of the skin may occur, start with one application daily, then gradually increase to two or three times daily if needed or as directed by a doctor
- if bothersome dryness or peeling occurs, reduce application to once a day or every other day.
- if going outside, apply sunscreen after using this product. If irritation or sensitivity develops, stop use of both products and ask a doctor.
- Sensitivity Test for a New User. Apply product sparingly to one or two small affected areas during the first 3 days. If no discomfort occurs, follow the directions stated above.

Other information

- THIS PRODUCT MAY BLEACH HAIR OR DYED FABRICS
- KEEP TIGHTLY CLOSED
- avoid storing at temperatures above 100°F (38°C)

Inactive Ingredients

water, glycerin, butylene glycol, carbomer, chlorphenesin, citric acid, dimethyl isosorbide, disodium EDTA, hyaluronic acid, hydrolyzed algin, lauryl methacrylate/glycol dimethacrylate crosspolymer, PEG/PPG-4/12 dimethicone, phenoxyethanol, phytic acid, portulaca oleracea extract, silanetriol, sodium citrate, sodium hydroxide, xanthan gum, zinc sulfate

Questions?1-877-636-2677

MON-FRI 9AM-5PM (EST)